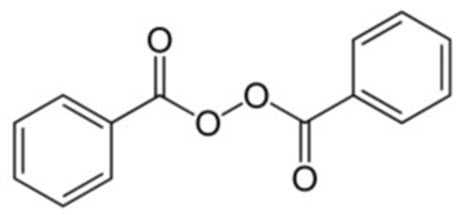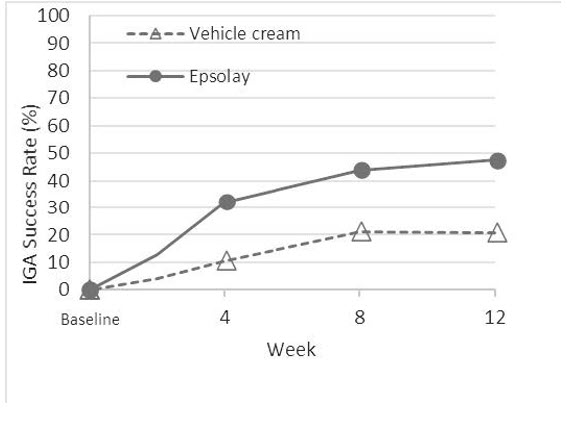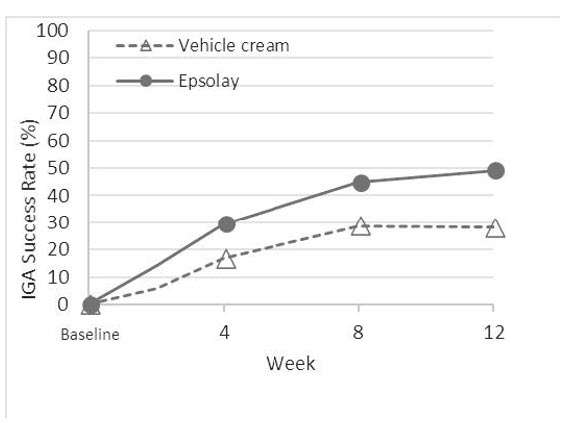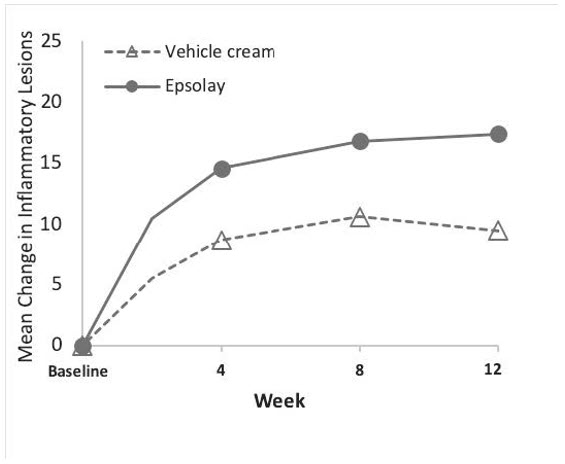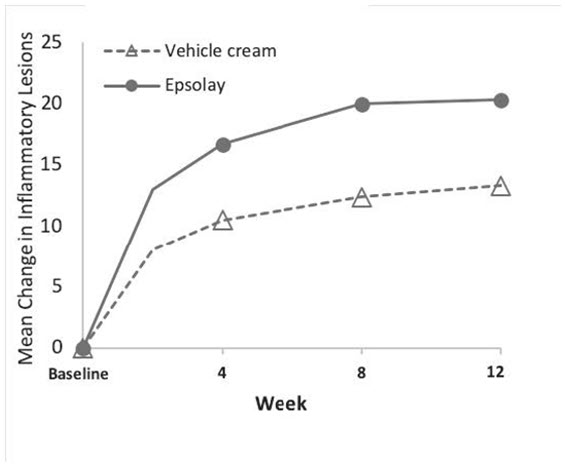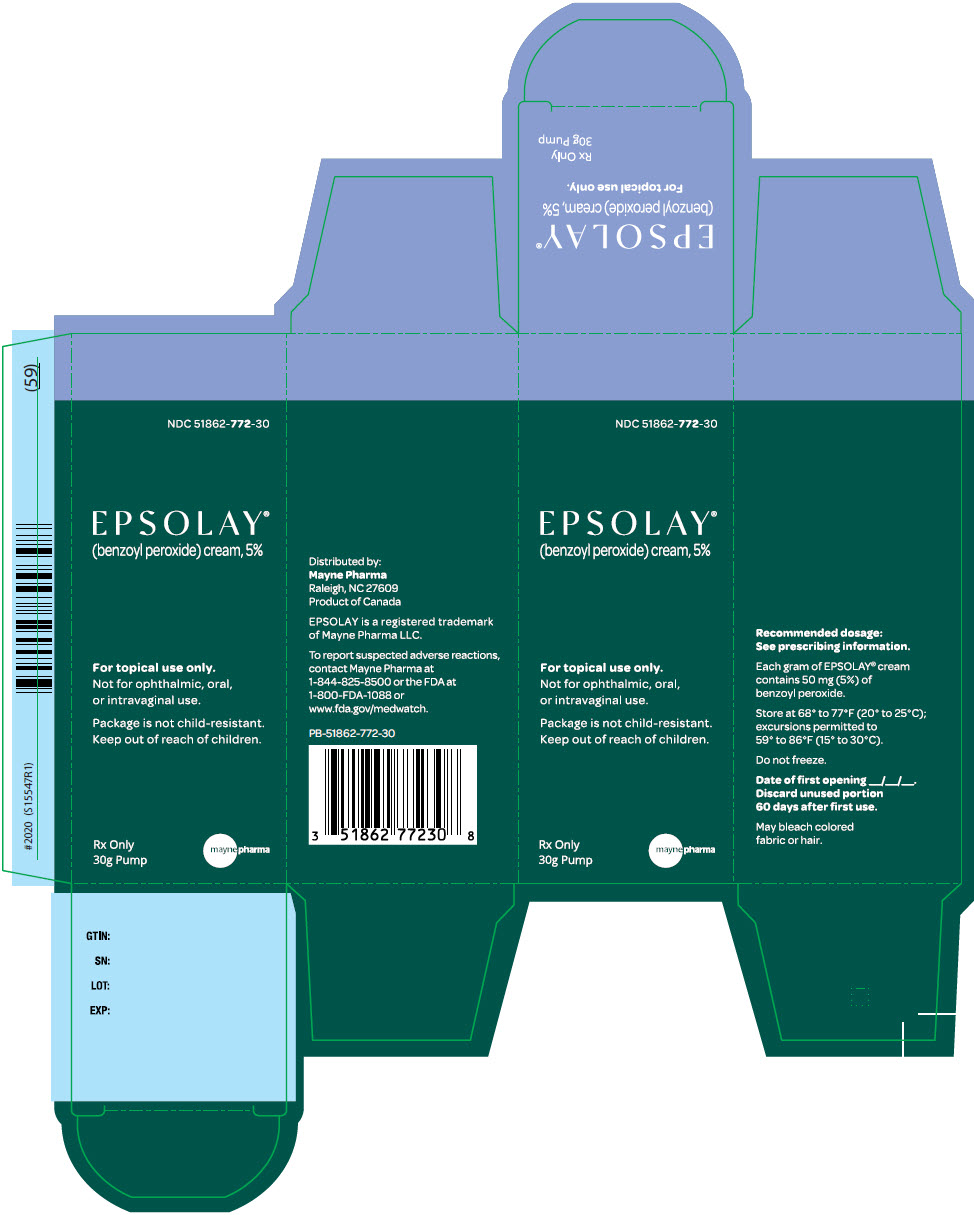 DRUG LABEL: Epsolay
NDC: 51862-772 | Form: CREAM
Manufacturer: Mayne Pharma Commercial LLC
Category: prescription | Type: HUMAN PRESCRIPTION DRUG LABEL
Date: 20250811

ACTIVE INGREDIENTS: Benzoyl Peroxide 30 mg/1 g
INACTIVE INGREDIENTS: ANHYDROUS CITRIC ACID; CETRIMONIUM CHLORIDE; CETYL ALCOHOL; CYCLOMETHICONE; EDETATE DISODIUM; GLYCERIN; GLYCERYL MONO- AND DIPALMITOSTEARATE; HYDROCHLORIC ACID; LACTIC ACID, UNSPECIFIED FORM; PEG-100 STEARATE; PHENOXYETHANOL; POLYQUATERNIUM-7 (70/30 ACRYLAMIDE/DADMAC; 1600000 MW); SILICON DIOXIDE; SODIUM HYDROXIDE; WATER

HIGHLIGHTS OF PRESCRIBING INFORMATION

These highlights do not include all the information needed to use EPSOLAY safely and effectively. See full prescribing information for EPSOLAY.
EPSOLAY® (benzoyl peroxide) cream, for topical use
Initial U.S. Approval: 1984

1 INDICATIONS AND USAGE

EPSOLAY is indicated for the treatment of inflammatory lesions of rosacea in adults. (1)

2 DOSAGE AND ADMINISTRATION

- Apply to the affected areas once daily. (2)
- Wash hands after application. (2)
- Not for oral, ophthalmic, or intravaginal use. (2)

3 DOSAGE FORMS AND STRENGTHS

Cream, 5%. (3)

4 CONTRAINDICATIONS

A history of a serious hypersensitivity reactions to benzoyl peroxide or any component of the formulation in EPSOLAY. (4)

5 WARNINGS AND PRECAUTIONS

- Hypersensitivity: Severe hypersensitivity reactions, including anaphylaxis and angioedema, have been reported with the use of benzoyl peroxide products. (5.1)
- Skin irritation/contact dermatitis: Erythema, scaling, dryness, stinging/burning, irritation and allergic contact dermatitis may occur with use of EPSOLAY and may necessitate discontinuation. (5.2)
- Photosensitivity: Avoid or minimize exposure to natural or artificial sunlight and use sun protection measures. (5.3)

6 ADVERSE REACTIONS

- Most common adverse reactions (incidence ≥ 1%) are application site reactions: pain, erythema, pruritis and edema. (6.1)

To report SUSPECTED ADVERSE REACTIONS, contact Mayne Pharma at 1-844-825-8500 or FDA at 1-800-FDA-1088 or www.fda.gov/medwatch.

FULL PRESCRIBING INFORMATION

1 INDICATIONS AND USAGE

EPSOLAY is indicated for the treatment of inflammatory lesions of rosacea in adults.

2 DOSAGE AND ADMINISTRATION

- Before initial use, prime the pump until the first drop of cream is released.
- Apply a pea-sized amount of EPSOLAY once daily in a thin layer to each area of the face (forehead, chin, nose, each cheek) on clean and dry skin. Avoid the eyes, lips and mouth.
- Wash hands after application.
- EPSOLAY may bleach hair or colored fabric.
- EPSOLAY is for topical use only. Not for oral, ophthalmic, or intravaginal use.
- Discard unused EPSOLAY 60 days after first use.

3 DOSAGE FORMS AND STRENGTHS

Cream, 5%. Each gram of EPSOLAY contains 50 mg of benzoyl peroxide in a white to off-white base.

4 CONTRAINDICATIONS

EPSOLAY is contraindicated in patients with a history of hypersensitivity reactions to benzoyl peroxide or any components of the formulation in EPSOLAY [see Warnings and Precautions (5.1)].

5 WARNINGS AND PRECAUTIONS

5.1 Hypersensitivity

Hypersensitivity reactions, including anaphylaxis, angioedema, and urticaria, have been reported with the use of benzoyl peroxide products. If a serious hypersensitivity reaction occurs, discontinue EPSOLAY immediately and initiate appropriate therapy.

5.2 Skin Irritation/Contact Dermatitis

Erythema, scaling, dryness and stinging/burning may be experienced with use of EPSOLAY. Irritation and contact dermatitis may occur. Apply a moisturizer and discontinue EPSOLAY if symptoms do not improve. Avoid application of EPSOLAY to cuts, abrasions, eczematous or sunburned skin.

5.3 Photosensitivity

Benzoyl peroxide may increase sensitivity to sunlight. Minimize or avoid exposure to natural or artificial sunlight (tanning beds or UVA/B treatment) while using EPSOLAY. Instruct the patient to implement sun protection measures (e.g., sunscreen and loose- fitting clothes) when sun exposure cannot be avoided. Discontinue EPSOLAY at the first evidence of sunburn.

6 ADVERSE REACTIONS

6.1 Clinical Trials Experience

Because clinical trials are conducted under widely varying conditions, adverse reaction rates observed in the clinical trials of a drug cannot be directly compared to rates in the clinical trials of another drug and may not reflect the rates observed in practice.

In two randomized, double-blind, vehicle-controlled trials, adult subjects with rosacea applied EPSOLAY (N = 488) or vehicle (N = 234) once daily for 12 weeks. The majority of subjects were Caucasian (93%) and female (73%) with a mean age of 51 years.

Table 1 presents the most common adverse reactions occurring in ≥ 1% of subjects treated with EPSOLAY and more frequently than in subjects treated with vehicle.

Table 1: Adverse Reactions Occurring in ≥ 1% of Subjects Treated with EPSOLAY and with Greater Frequency than Subjects Treated with Vehicle
 | EPSOLAY N=488 | Vehicle N=234
Application site pain | 11 (2%) | 2 (1%)
Application site erythema | 11 (2%) | 2 (1%)
Application site pruritus | 6 (1%) | 1 (<1%)
Application site edema [Application site edema includes: application site swelling and application site edema] | 4 (1%) | 0 (0%)

During the clinical trials, local tolerability evaluations were conducted at baseline and at each study visit by assessment of dryness, itching, scaling and stinging/burning. Table 2 presents the local tolerability assessments by severity grade at Week 12.

Table 2: Facial Cutaneous Tolerability Assessment
Sign/Symptom | EPSOLAY N=455 [Of the 488 subjects treated with EPSOLAY, 455 subjects had local tolerability assessments at Week 12.]
Sign/Symptom | Severity at Week 12
Sign/Symptom | Mild | Moderate | Severe
Dryness | 25% | 7% | 0%
Itching | 24% | 6% | 0%
Scaling | 13% | 4% | 0%
Stinging/Burning | 20% | 3% | 1%

In a 40-week open-label extension safety study (for a total of up to 52 weeks of treatment) the frequency and severity of local tolerability signs and symptoms at Week 52 were comparable to those reported at Week 12.

8 USE IN SPECIFIC POPULATIONS

8.1 Pregnancy

Risk Summary

The systemic exposure of benzoyl peroxide is unknown. Based on the published literature, benzoyl peroxide is metabolized to benzoic acid (an endogenous substance), which is eliminated in the urine. Hence, maternal use is not expected to result in fetal exposure to the drug. Animal reproductive studies have not been conducted with EPSOLAY or benzoyl peroxide.

The background risk of major birth defects and miscarriage for the indicated population is unknown. All pregnancies have a background risk of birth defect, loss, or other adverse outcomes. In the U.S. general population, the estimated background risk of major birth defects and miscarriage in clinically recognized pregnancies is 2 to 4% and 15 to 20%, respectively.

8.2 Lactation

Risk Summary

There are no data on the presence of benzoyl peroxide in human milk, its effects on the breastfed infant or its effects on milk production. The systemic exposure of benzoyl peroxide is unknown. Based on the published literature, benzoyl peroxide is metabolized to benzoic acid (an endogenous substance), which is eliminated in the urine. Any amount of benzoyl peroxide excreted into human milk by a nursing mother would be expected to be metabolized by tissue and stomach esterases. Therefore, breastfeeding is not expected to result in exposure of the infant to EPSOLAY. The developmental and health benefits of breastfeeding should be considered along with the mother's clinical need for EPSOLAY and any potential adverse effects on the breastfed child from EPSOLAY or from the underlying maternal condition.

8.4 Pediatric Use

Safety and effectiveness of EPSOLAY for the treatment of inflammatory lesions of rosacea have not been established in pediatric patients.

8.5 Geriatric Use

Of the 733 subjects in the clinical trials of EPSOLAY, 127 (17%) subjects were 65 and over, while 37 (3%) subjects were 75 and over. No overall differences in safety or effectiveness were observed between these subjects and younger subjects.

11 DESCRIPTION

EPSOLAY (benzoyl peroxide) cream is for topical use. Each gram of EPSOLAY contains 50 mg of benzoyl peroxide.

The chemical name for benzoyl peroxide is benzoyl benzenecarboperoxoate. It has the following structural formula:

Molecular Formula: C14H10O4

Molecular Weight: 242.23

The benzoyl peroxide in EPSOLAY is in a solid form that is incorporated into a microcapsule composed of silicon dioxide, cetrimonium chloride and polyquaternium-7.

EPSOLAY contains anhydrous citric acid, cetrimonium chloride, cetyl alcohol, cyclomethicone, edetate disodium, glycerin, hydrochloric acid, lactic acid, macrogol stearate Type I, mono and di-glycerides, phenoxyethanol, polyquaternium-7, purified water, silicon dioxide and sodium hydroxide as inactive ingredients.

12 CLINICAL PHARMACOLOGY

12.1 Mechanism of Action

Benzoyl peroxide is an oxidizing agent with bactericidal and keratolytic effects but the precise mechanism of action in the treatment of rosacea is unknown.

12.2 Pharmacodynamics

The pharmacodynamics of EPSOLAY in the treatment of rosacea are unknown.

12.3 Pharmacokinetics

Benzoyl peroxide is absorbed by the skin where it is converted to benzoic acid, an endogenous substance, which is eliminated in the urine. The systemic exposure of benzoyl peroxide following the application of EPSOLAY was not assessed.

13 NONCLINICAL TOXICOLOGY

13.1 Carcinogenesis, Mutagenesis, Impairment of Fertility

Carcinogenicity, mutagenicity, and impairment of fertility studies were not conducted with EPSOLAY.

The role of benzoyl peroxide as a tumor promoter has been well established in several animal species. However, the significance of this finding in humans is unknown.

No significant increase in tumor formation was observed in rats treated topically with a 15 to 25% benzoyl peroxide carbopol gel (3 to 5 times the concentration of benzoyl peroxide in EPSOLAY) for two years. Similar results were obtained in mice topically treated with 25% benzoyl peroxide gel for 56 weeks followed by intermittent treatment with 15% benzoyl peroxide gel for rest of the 2 years study period and in mice topically treated with 5% benzoyl peroxide gel for two years.

Bacterial mutagenicity assays (Ames test) conducted with benzoyl peroxide have provided mixed results; mutagenic potential was observed in a few studies but not in a majority of investigations. Benzoyl peroxide has been found to cause DNA strand breaks in a variety of mammalian cell types and to cause sister chromatid exchanges in Chinese hamster ovary cells.

Fertility studies were not conducted with benzoyl peroxide.

14 CLINICAL STUDIES

The safety and efficacy of EPSOLAY was evaluated in two multicenter, randomized, double-blind, vehicle-controlled trials (Trial 1 [NCT03448939] and Trial 2 [NCT03564119]) in subjects with moderate-to-severe papulopustular rosacea. The trials were conducted in 733 subjects, aged 18 years and older. Subjects were treated once daily for 12 weeks with either EPSOLAY or vehicle cream.

Subjects were required to have a minimum of 15 to 70 total inflammatory lesions (papules and/or pustules) and no more than 2 nodules (where a nodule was defined as a papule or pustule greater than 5 mm in diameter) and an Investigator Global Assessment (IGA) score of 3 ("moderate") or 4 ("severe") at baseline. Overall, 93% of subjects were Caucasian, 73% were female, and the mean age was 51 years (ranged from 18 to 85 years). At baseline, subjects had a mean inflammatory lesion count of 27.5, 89% were scored as moderate (IGA=3), and 11% scored as severe (IGA=4).

The co-primary efficacy endpoints in both trials were the proportion of subjects with treatment success at Week 12, defined as an IGA score of 0 ("clear") or 1 ("almost clear") with at least a two-grade reduction from baseline, and the absolute change from baseline in inflammatory lesion counts at Week 12. The results at Week 12 are presented in Table 3. EPSOLAY was more effective than vehicle cream on the co-primary efficacy endpoints starting from 4 weeks of treatment in both trials, see Figure 1 through Figure 4.

Table 3: Efficacy Results of EPSOLAY in Subjects with Moderate to Severe Papulopustular Rosacea at Week 12
 | Trial 1 |  | Trial 2
 | Epsolay (N=243) | Vehicle (N=118) | Epsolay (N=250) | Vehicle (N=122)
IGA Treatment Success [Investigator Global Assessment (IGA) success was defined as an IGA score of 0 ("clear") or 1 ("almost clear") with at least a two-grade reduction from baseline.] | 47.4% | 20.7% | 49.2% | 28.2%
Difference from Vehicle (95% Cl) | 26.7% (16.7%, 36.8%) |  | 21.0% (10.7%, 31.3%)
Inflammatory Lesions
Mean [Means presented in table are Least Square (LS) Means.] Absolute Change | -17.4 | -9.5 | -20.3 | -13.3
Difference from Vehicle (95% Cl) | -7.9 (-10.0, -5.9) |  | -6.9 (-9.0, -4.9)
Mean Percent Change | -68.2% | -38.3% | -69.4% | -46.0%
Difference from Vehicle (95% Cl) | -29.9% (-37.8%, -22.0%) |  | -23.4% (-30.5%, -16.3%)

Figure 1: IGA Success Rate Over Time in Trial 1

Figure 2: IGA Success Rate Over Time in Trial 2

Figure 3: Mean Absolute Change in Inflammatory Lesion Counts fromBaseline Over Time in Trial 1

Figure 4: Mean Absolute Change in Inflammatory Lesion Counts from Baseline Over Time in Trial 2

16 HOW SUPPLIED/STORAGE AND HANDLING

How Supplied

EPSOLAY is a white to off-white cream supplied in an airless pump as follows: 30 gram pump: NDC 51862-772-30

Storage and Handling

- Store at 20°C to 25°C (68°F to 77°F) with excursions permitted to 15°C to 30°C (59°F to 86°F) [see USP Controlled Room Temperature].
- Keep away from heat.
- Do not freeze.
- Discard unused cream 60 days after first use.

17 PATIENT COUNSELING INFORMATION

Advise the patient to read the FDA-approved patient labeling (Patient Information).

Hypersensitivity

Inform patients that serious hypersensitivity reactions occurred with the use of benzoyl peroxide products. If a patient experiences a serious hypersensitivity reaction, instruct patient to discontinue EPSOLAY immediately and seek medical help [see Warnings and Precautions (5.1)].

Skin Irritation/Contact Dermatitis

Inform patients that EPSOLAY may cause irritation such as erythema, scaling, dryness, stinging or burning. Advise the patient to use a moisturizer for irritation [see Warnings and Precautions (5.2)].

Photosensitivity

Advise patients to minimize or avoid exposure to natural or artificial light (tanning beds or UVA/B treatment) and to use sun protective measures, if patients need to be outdoors while using EPSOLAY [see Warnings and Precautions (5.3)].

Administration Instructions

Advise patients to apply EPSOLAY exactly as directed in a thin layer, avoiding the eyes, lips and mouth and to wash hands immediately after application. Inform patients that EPSOLAY may bleach hair or colored fabric [see Dosage and Administration (2)].

Distributed by:
Mayne Pharma
Raleigh, NC 27609
Product of Canada
All trademarks are the property of their respective owners.
IN-51862-772-30

PATIENT INFORMATION EPSOLAY ® (ep' soe lay) (benzoyl peroxide) cream

Important: EPSOLAY is for use on the skin only (topical). Do not use EPSOLAY in or on your mouth, eyes or vagina.

What is EPSOLAY?

EPSOLAY is a prescription medicine used on the skin (topical) to treat adults with pimples and bumps caused by a condition called rosacea.

It is not known if EPSOLAY is safe and effective in children.

Do not use EPSOLAY if you have had an allergic reaction to benzoyl peroxide or any of the ingredients in EPSOLAY. See the end of this leaflet for a complete list of ingredients in EPSOLAY.

Before using EPSOLAY, tell your healthcare provider about all of your medical conditions, including if you:

- have other skin problems, including eczema, cuts, or sunburn.
- are pregnant or plan to become pregnant. It is not known if EPSOLAY will harm your unborn baby.
- are breastfeeding or plan to breastfeed. It is not known if EPSOLAY passes into your breast milk. Talk to your healthcare provider about the best way to feed your baby during treatment with EPSOLAY.

Tell your healthcare provider about all the medicines you take, including prescription and over-the-counter medicines, vitamins, and herbal supplements.

How should I use EPSOLAY?

- Use EPSOLAY exactly as your healthcare provider tells you.
- Apply EPSOLAY to your face 1 time each day on clean and dry skin.
- Before you use EPSOLAY for the first time, prime the pump by pressing down until the first drop of cream is released.
- Use the pump to dispense a pea-size amount of EPSOLAY onto your fingertip. Spread a thin layer over each area of your face (forehead, chin, nose, each cheek). Avoid contact with your eyes, lips and mouth.
- Wash your hands right away after applying EPSOLAY.

What should I avoid while using EPSOLAY?

- Avoid using EPSOLAY on skin areas with cuts, abrasions, eczema, or on sunburned skin.
- Limit your time in sunlight. Avoid sunlight or artificial sunlight such as sunlamps or tanning beds. EPSOLAY may make your skin more sensitive to the sun and the light from sunlamps and tanning beds. Use sun protection measures such as sunscreen and wear loose-fitting clothes that cover your skin while out in sunlight. Stop using EPSOLAY if you get sunburn.
- Avoid getting EPSOLAY in your hair or on colored fabric. EPSOLAY may bleach hair or colored fabric.

What are the possible side effects of EPSOLAY? EPSOLAY may cause serious side effects, including:

- Allergic reactions. Stop using EPSOLAY and get medical help right away if you have any of the following symptoms during treatment with EPSOLAY:
  - hives, rash or severe itching
  - swelling of your face, eyes, lips, tongue, or throat
  - trouble breathing or throat tightness
  - feeling faint, dizzy, or lightheaded
- Skin irritation. EPSOLAY may cause skin irritation such as redness, scaling, dryness, stinging, or burning. You may use a moisturizer if you develop skin irritation. Tell your healthcare provider if your symptoms do not improve, you may need to stop treatment with EPSOLAY.
- Sensitivity to sunlight. See "What should I avoid while using EPSOLAY?"

The most common side effects of EPSOLAY include pain, redness, itching, and swelling at application site.

These are not all the possible side effects with EPSOLAY.

Call your doctor for medical advice about side effects. You may report side effects to FDA at 1-800-FDA-1088.

How should I store EPSOLAY?

- Store EPSOLAY at room temperature between 68°F to 77°F (20°C to 25°C).
- Keep EPSOLAY away from heat.
- Do not freeze EPSOLAY
- Throw away (discard) unused EPSOLAY 60 days after first use.

Keep EPSOLAY and all medicines out of the reach of children.

General information about the safe and effective use of EPSOLAY.

Medicines are sometimes prescribed for purposes other than those listed in a Patient Information leaflet. Do not use EPSOLAY for a condition for which it was not prescribed. Do not give EPSOLAY to other people, even if they have the same symptoms that you have. It may harm them. You can ask your pharmacist or healthcare provider for information about EPSOLAY that is written for health professionals.

What are the ingredients in EPSOLAY?
Active ingredient: benzoyl peroxide

Inactive ingredients: anhydrous citric acid, cetrimonium chloride, cetyl alcohol, cyclomethicone, edetate disodium, glycerin, hydrochloric acid, lactic acid, macrogol stearate Type I, mono and di-glycerides, phenoxyethanol, polyquaternium-7, purified water, silicon dioxide and sodium hydroxide.

Distributed by:
Mayne Pharma
Raleigh, NC 27609
Product of Canada
EPSOLAY is a registered trademark of Mayne Pharma LLC.
IN-51862-772-30

For more information, go to www.EPSOLAY.com or call Mayne Pharma at 1-844-825-8500.

This Patient Information has been approved by the U.S. Food and Drug Administration. Issued: 02/2025

PRINCIPAL DISPLAY PANEL - 30 g Bottle Carton

NDC 51862-772-30

EPSOLAY®
(benzoyl peroxide) cream, 5%

For topical use only.
Not for ophthalmic, oral,
or intravaginal use.

Package is not child-resistant.
Keep out of reach of children.

Rx Only
30g Pump

mayne pharma